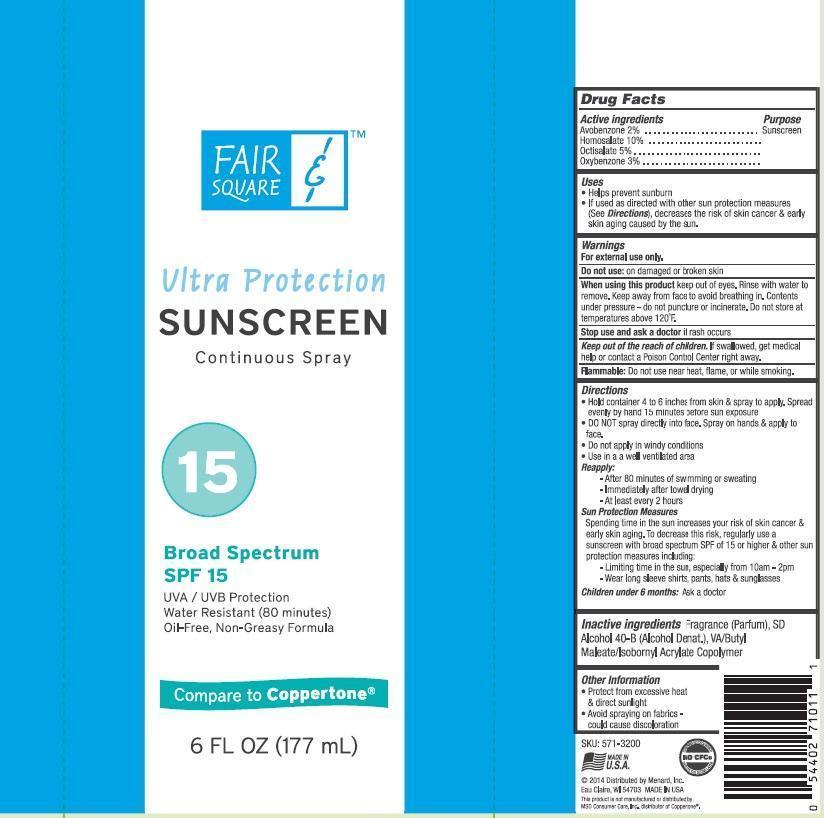 DRUG LABEL: Fair and Square
NDC: 13630-0080 | Form: AEROSOL, SPRAY
Manufacturer: Prime Packaging, Inc.
Category: otc | Type: HUMAN OTC DRUG LABEL
Date: 20200117

ACTIVE INGREDIENTS: AVOBENZONE 16.1 mg/1 mL; HOMOSALATE 80.3 mg/1 mL; OCTISALATE 40.2 mg/1 mL; OXYBENZONE 24.1 mg/1 mL
INACTIVE INGREDIENTS: ALCOHOL; BUTYL MALEURATE; ISOBORNYL ACRYLATE

Active ingredients

Avobenzone 2%, Homosalate 10%, Octisalate 5 %, and Oxybenzone 3 %

Purpose

Sunscreen

Uses

- helps prevent sunburn
- If use as directed with other sun protection measures (see Directions), decreases the risk of skin cancer & early skin aging caused by the sun.

Warnings

OTHER SAFETY INFORMATION

For external use only

Do not use: on damaged or broken skin

When using this product keep out of eyes. Rinse with water to remove. Keep away from face to avoid breathing it. Content is under pressure - do not pumcture or incinerate. Do not store at temperature above 120°F.

Stop use and ask a doctor if rash occurs

Keep out of reach of children. If product is swallowed, get medical help or contact a Poison Control Center right away.

OTHER SAFETY INFORMATION

Flammable: Do not use near heat, flame or while smoking.

Directions

- Hold container 4-6 inches from the skin & spray to apply. Spread evenly by hand 15 minuted before sun exposure
- DO NOT spray directly into face. Spray on hands then apply to face.
- Do not apply in windy conditions.
- Use in a well-ventilated area

Reapply:

- After 80 minutes of swimming or sweating
- immediately after towel drying
- at least every 2 hours

Sun Protection Measures

Spending time in the sun increases your risk of skin cancer & early aging. To decrease this risk, regularly use a sunscreen with a broad spectrum SPF 15 or higher and othre sun protection measures including:

- limit time in the sun, especially from 10am - 2 pm
- wear long-sleeve shirts, pants, hats, and sunglasses

Children under 6 months: Ask a doctor

Inactive ingredients

Fragrance (Parfum), SD Alcohol 40-B (Alcohol Denat.), VA/Butyl Maleate/Isobornyl Acrylate Copolymer

Other Information

- Protect this product from exessive heat and direct sunlight
- avoid spraying on fabrics - could cause discoloration

PRINCIPAL DISPLAY PANEL - 177 mL Can Label

Fair

&

Square

Ultra Protection

Sunscreen

Continuous Spray

15

Broad Spectrum

SPF 15

UVA/UVB Protection

Water Resistant (80 Minutes)

Oil-Free, Non-Greasy Formula

Compare to Coppertone

6 FL OZ (177 mL)